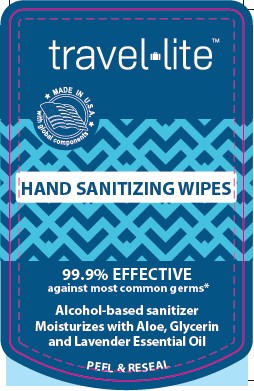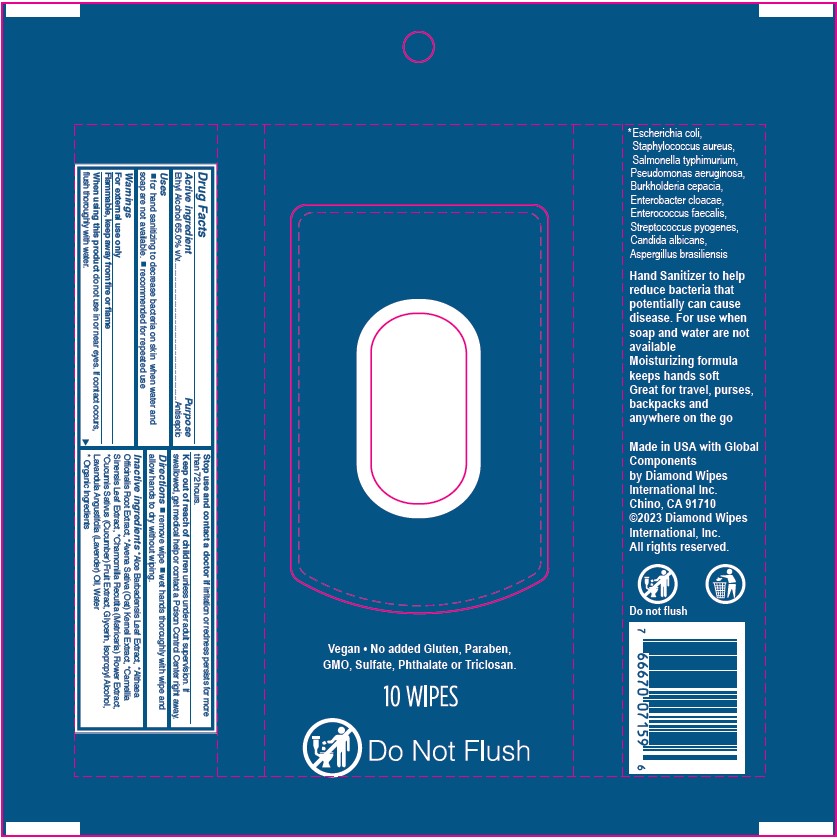 DRUG LABEL: Travel lite Hand Sanitizing Wipes
NDC: 64709-157 | Form: CLOTH
Manufacturer: Diamond Wipes International, Inc
Category: otc | Type: HUMAN OTC DRUG LABEL
Date: 20231201

ACTIVE INGREDIENTS: ALCOHOL 65 mL/100 mL
INACTIVE INGREDIENTS: ALOE VERA LEAF; ALTHAEA OFFICINALIS ROOT; WATER; OAT; GREEN TEA LEAF; CHAMOMILE; CUCUMBER; GLYCERIN; ISOPROPYL ALCOHOL; LAVENDER OIL

Travel Lite Hand Sanitizing Wipes

Active ingredient

Ethyl Alcohol 65.0% v/v

Purpose

Antimicrobial

Uses

■ for hand sanitizing to decrease bacteria on skin when water and soap are not available.

■ recommended for repeated use

Warnings

For external use only

Flammable, keep away from fire or flame

When using this product do not use in or near eyes. If contact occurs, flush thoroughly with water.

Stop use and contact a doctor if irritation or redness persists for more than 72 hours.

Keep out of each of children

Keep out of reach of children unless under adult supervision. If swallowed, get medical help or contact a Poison Control Center right away.

Directions

■ remove wipe ■ wet hands thoroughly with wipe and allow hands to dry without wiping.

Inactive ingredients

*Aloe Barbadensis Leaf Extract, *Althaea Officinalis Root Extract, *Avena Sativa (Oat) Kernel Extract, *Camellia Sinensis Leaf Extract, *Chamomilla Recutita (Matricaria) Flower Extract, *Cucumis Sativus (Cucumber) Fruit Extract, Glycerin, Isopropyl Alcohol, Lavandula Angustifolia (Lavender) Oil, Water

* Organic Ingredients

Label

travel lite™

MAKE IN U.S.A. with global components

HAND SANITIZING WIPES

99.9% EFFECTIVE against most common germs*

Alcohol-based sanitizer

Moisturizes with Aloe, Glycerin

and Lavender Essential Oil

PEEL & RESEAL

Vegan • No added Gluten, Paraben, GMO, Sulfate, Phthalate or Triclosan.

10 WIPES

Do Not Flush

* Escherichia coli, Staphylococcus aureus, Salmonella typhimurium, Pseudomonas aeruginosa, Burkholderia cepacia, Enterobacter cloacae, Enterococcus faecalis, Streptococcus pyogenes, Candida albicans, Aspergillus brasiliensis

Hand Sanitizer to help reduce bacteria that potentially can cause disease. For use when soap and water are not available Moisturizing formula keeps hands soft Great for travel, purses, backpacks and anywhere on the go

Made in USA with Global Components by Diamond Wipes International Inc.

Chino, CA 91710 ©2023 Diamond Wipes International, Inc. All rights reserved.

Do not flush

UPC 7 6667007159 6

Drug Facts

Active Ingredient Purpose

Ethyl Alcohol 65.0% v/v..............................Antimicrobial

Uses

■ for hand sanitizing to decrease bacteria on skin when water and soap are not available.

■ recommended for repeated use

Warnings

For external use only

Flammable, keep away from fire or flame

When using this product do not use in or near eyes. If contact occurs, flush thoroughly with water.

Stop use and contact a doctor if irritation or redness persists for more than 72 hours.

Keep out of reach of children unless under adult supervision. If swallowed, get medical help or contact a Poison Control Center right away.

Discontinue ■ remove wipe ■ wet hands thoroughly with wipe and allow hands to dry without wiping.

Inactive ingredients*Aloe Barbadensis Leaf Extract, *Althaea Officinalis Root Extract, *Avena Sativa (Oat) Kernel Extract, *Camellia Sinensis Leaf Extract, *Chamomilla Recutita (Matricaria) Flower Extract, *Cucumis Sativus (Cucumber) Fruit Extract, Glycerin, Isopropyl Alcohol, Lavandula Angustifolia (Lavender) Oil, Water

* Organic Ingredients